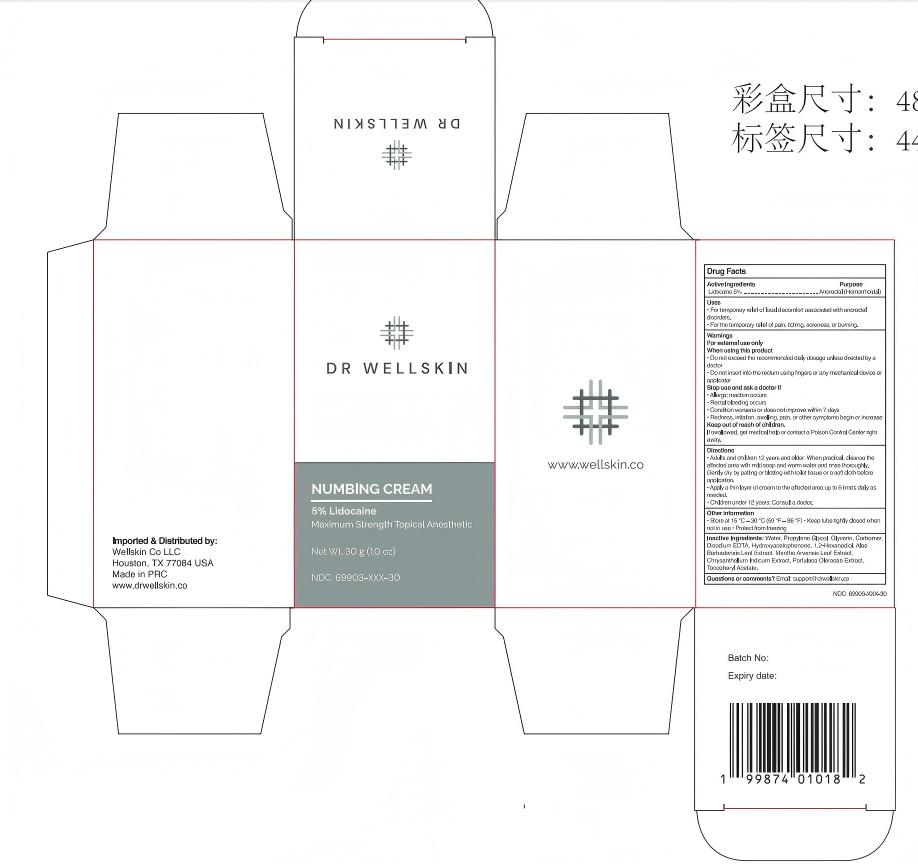 DRUG LABEL: Dr Wellskin Numbing Cream
NDC: 84019-042 | Form: CREAM
Manufacturer: Shengnan (Guangzhou) Cosmetics Co., LTD
Category: otc | Type: HUMAN OTC DRUG LABEL
Date: 20260112

ACTIVE INGREDIENTS: LIDOCAINE 40 mg/1 g
INACTIVE INGREDIENTS: CARBOMER; 1,2-HEXANEDIOL; HYDROXYACETOPHENONE; GLYCERIN; WATER

Dr Wellskin Numbing Cream
30g/1.0 oz e

WARNINGS

For external use only.

PURPOSE

Topical Anesthetic

STOP USE

Allergic reaction occurs.
Rectal bleeding occurs.
Condition worsens or does not improve within 7 days.
Redness, irritation, sweling, pain, or other symptoms begin or increase.

ACTIVE INGREDIENT

4% Lidocaine

WHEN USING

Do not exceed the recommended daily dosage unless directed by adoctor
Do not insert into the rectum using fingers or any mechanical device orapplicator

INACTIVE INGREDIENT

Water, Propylene Glycol, Glycerin, Carbomer, Disodium EDTA, Hydroxyacetophenone, 1,2-Hexanediol, Aloe Barbadensis Leaf Extract, Mentha Arvensis Leaf Extract, Chrysanthellum Indicum Extract, Portulaca Oleracea Extract,Tocopheryl Acetate.

DOSAGE AND ADMINISTRATION

Adults and children 12
years and older: Apply a
thin layer to the affected
area 1-3 times daily or
as directed by a
healthcare provider.

INDICATIONS AND USAGE

Adults and children 12 years and older: When practical, cleanse theaffected area with mild soap and warm water and rinse thoroughly.Gently dry by patting or blotting with toilet tissue or a soft cloth before application.
Apply a thin layer of cream to the affected area up to 6 times daily as needed.
Children under 12 years: Consult a doctor.

KEEP OUT OF REACH OF CHILDREN

If swallowed, get medical help or contact a Poison Control Center right
away.